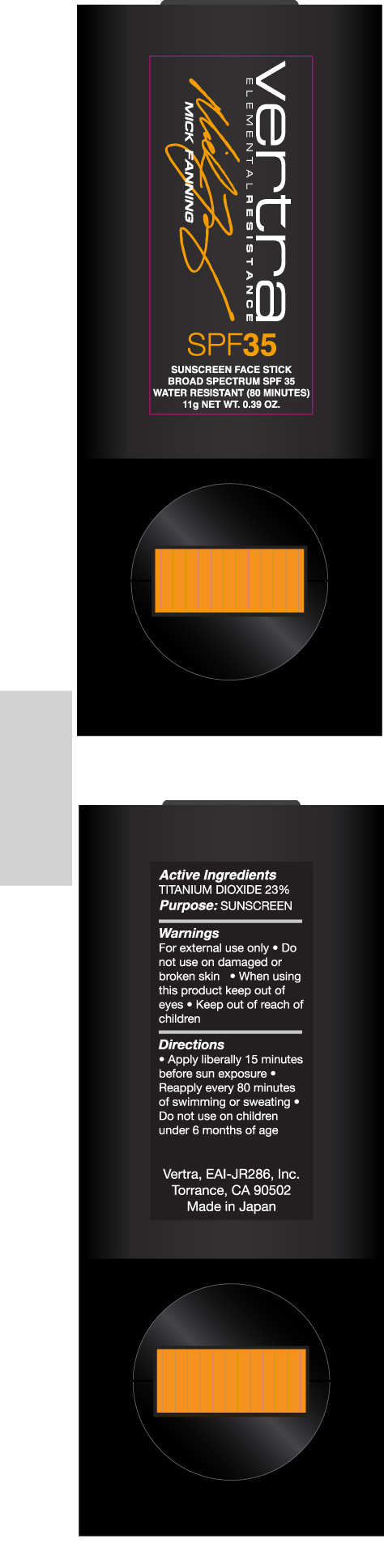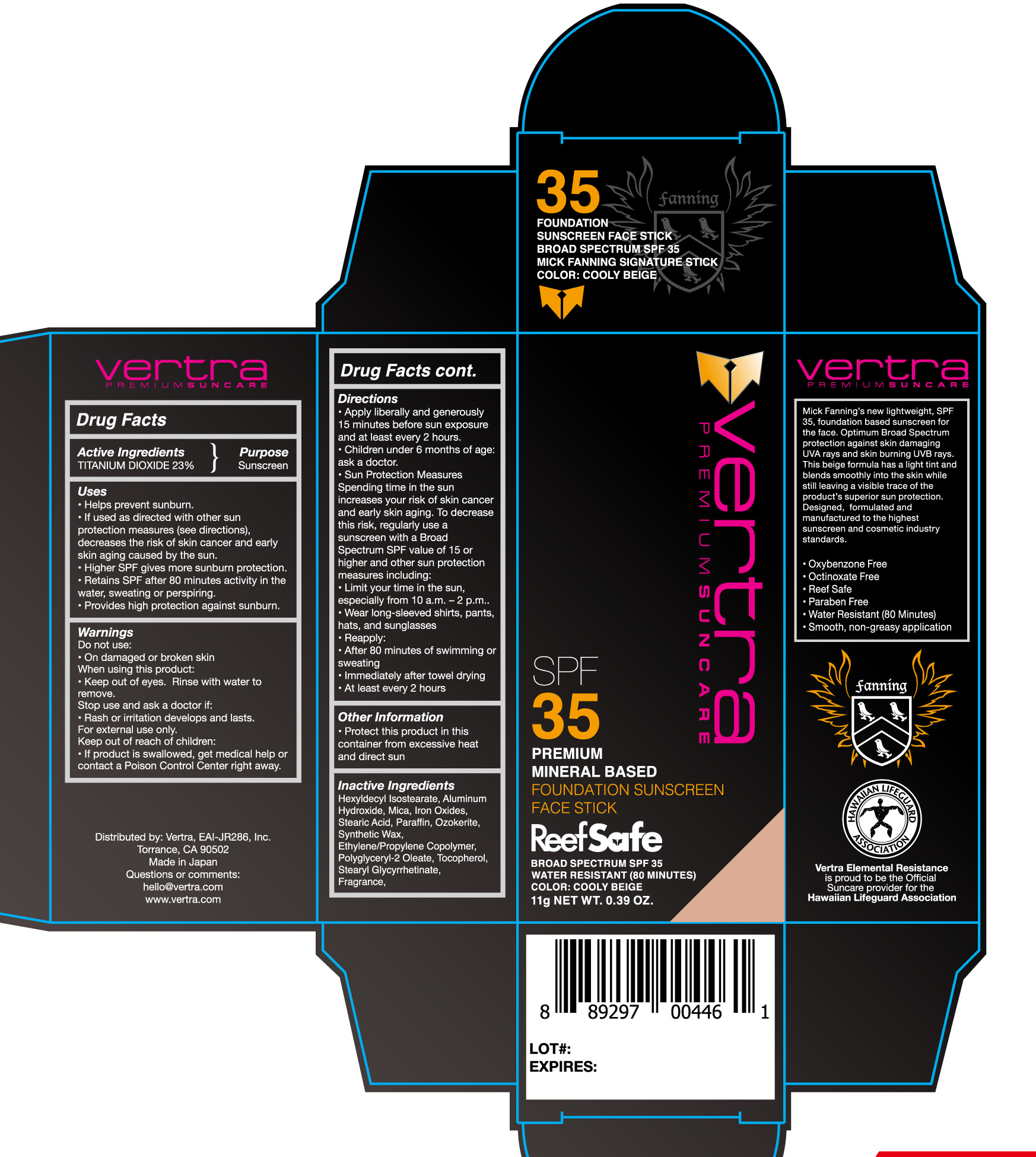 DRUG LABEL: Foundation Sunscreen Face Stick Broad Spectrum SPF 35 Cooly Beige
NDC: 71014-021 | Form: STICK
Manufacturer: Eai-Jr286, Inc.
Category: otc | Type: HUMAN OTC DRUG LABEL
Date: 20200708

ACTIVE INGREDIENTS: TITANIUM DIOXIDE 23 g/100 g
INACTIVE INGREDIENTS: ALUMINUM HYDROXIDE; HEXYLDECYL ISOSTEARATE; FERRIC OXIDE RED; FERRIC OXIDE YELLOW; FERROSOFERRIC OXIDE; MICA; CERESIN; PARAFFIN; STEARIC ACID; SYNTHETIC WAX (1200 MW); TOCOPHEROL; STEARYL GLYCYRRHETINATE

Foundation Sunscreen Face Stick Broad Spectrum SPF 35 Cooly Beige

Active Ingredients Purpose

Titanium Dioxide 23% Sunscreen

Uses

- helps prevent sunburn
- if used as directed with other sun protection measures (see Directions), decreases the risk of skin cancer and early skin aging caused by the sun
- Higher SPF gives more sunburn protection
- Retains SPF after 80 minutes activity in the water, sweating, or perspiring.
- Provides high protection against sunburn

KEEP OUT OF REACH OF CHILDREN

Keep out of reach of chilcren. If product is swallowed, get medical help or contact a Poison Control Center right away.

Stop use and ask a doctor if rash or irritation develops and lasts

Warnings

For external use only

- Do not use on damaged or broken skin
- When using this product keep out of eyes
- Rinse with water to remove

Directions

- apply liberally and evenly 15 minutes before sun exposure
- apply to all skin exposed to sun
- use a water resistant sunscreen if swimming or sweating
- reapply: after 80 minutes of swimming or sweating
- immediately after towel drying
- at leasty every 2 hours
- Sun Protection Measures. Spending time in the sun increases your risk of skin cancer and early skin aging. To decrease this risk, regularly use a sunscreen with a Broad Spectrum SPF value 15 or higher and other sun protection measures including:
- limit time in the sun, especially from 10 a.m. - 2 p.m.
- wear long-sleeve shirts, pants, hats, and sunglasses
- children under 6 months of age: ask a doctor

INACTIVE INGREDIENT

Hexyldecyl Isostearate, Aluminum Hydroxide, Mica, Iron oxides, Stearic Acid, Paraffin, Ozokerite, Synthetic Wax, Ethylene/Propylene Copolymer, Polyglyceryl-2 Oleate, Tocopherol, Stearyl Glycyrrhetinate, Fragrance

PACKAGE LABEL

Vertra Premium Suncare

Foundation
Sunscreen Face Stick
Broad Spectrum SPF 35
Water Resistant (80 minutes)

Color: Cooly Beige

11g NET WT. .39 OZ.